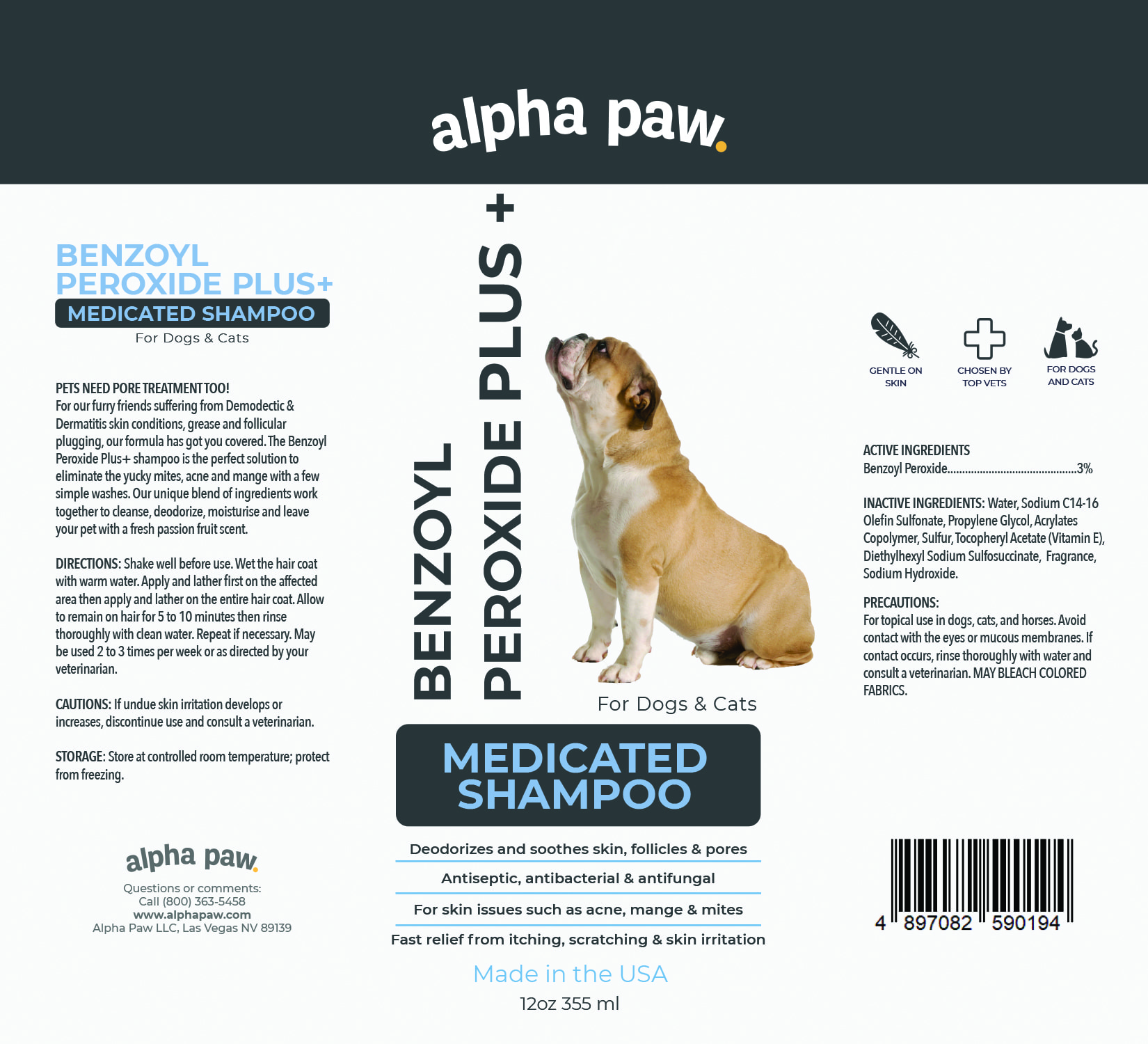 DRUG LABEL: BENZOYL PEROXIDE PLUS MEDICATED
NDC: 86175-004 | Form: SHAMPOO
Manufacturer: Alpha Paw Inc
Category: animal | Type: OTC ANIMAL DRUG LABEL
Date: 20230316

ACTIVE INGREDIENTS: BENZOYL PEROXIDE 3 g/100 mL
INACTIVE INGREDIENTS: WATER; SODIUM C14-16 OLEFIN SULFONATE; PROPYLENE GLYCOL; BUTYL ACRYLATE/METHYL METHACRYLATE/METHACRYLIC ACID COPOLYMER (18000 MW); SULFUR; .ALPHA.-TOCOPHEROL ACETATE; DOCUSATE SODIUM; SODIUM HYDROXIDE

BENZOYL PEROXIDE PLUS MEDICATED SHAMPOO

ACTIVE INGREDIENTS
Benzoyl Peroxide............................................3%

PURPOSE

BENZOYL PEROXIDE PLUS+ MEDICATED SHAMPOO For Dogs & Cats

PETS NEED PORE TREATMENT TOO!

For our furry friends suffering from Demodectic & Dermatitis skin conditions, grease and follicular plugging, our formula has got you covered. The Benzoyl Peroxide Plus+ shampoo is the perfect solution to eliminate the yucky mites, acne and mange with a few simple washes. Our unique blend of ingredients work together to cleanse, deodorize, moisturise and leave your pet with a fresh passion fruit scent.

INACTIVE INGREDIENTS

Water, Sodium C14-16 Olefin Sulfonate, Propylene Glycol, Acrylates Copolymer, Sulfur, Tocopheryl Acetate (Vitamin E), Diethylhexyl Sodium Sulfosuccinate, Fragrance, Sodium Hydroxide.

PRECAUTIONS

For topical use in dogs, cats, and horses. Avoid contact with the eyes or mucous membranes. If contact occurs, rinse thoroughly with water and consult a veterinarian. MAY BLEACH COLORED FABRICS.

DIRECTIONS

Shake well before use. Wet the hair coat with warm water. Apply and lather first on the affected area then apply and lather on the entire hair coat. Allow to remain on hair for 5 to 10 minutes then rinse thoroughly with clean water. Repeat if necessary. May be used 2 to 3 times per week or as directed by your veterinarian.

CAUTIONS

If undue skin irritation develops or increases, discontinue use and consult a veterinarian.

STORAGE

Store at controlled room temperature.

Deodorizes and soothes skin, follicles & pores
Antiseptic, antibacterial & antifungal
For skin issues such as acne, mange & mites
Fast relief from itching, scratching & skin irritation

GENTLE ON SKIN
CHOSEN BY TOP VETS
FOR DOGS AND CATS

ALPHA PAW
Questions or Comments:
Call (800) 363-5458
www.alphapaw.com
Alpha Paw LLC, Las Vegas NV 89139

Packaging

Package 12oz 355mL